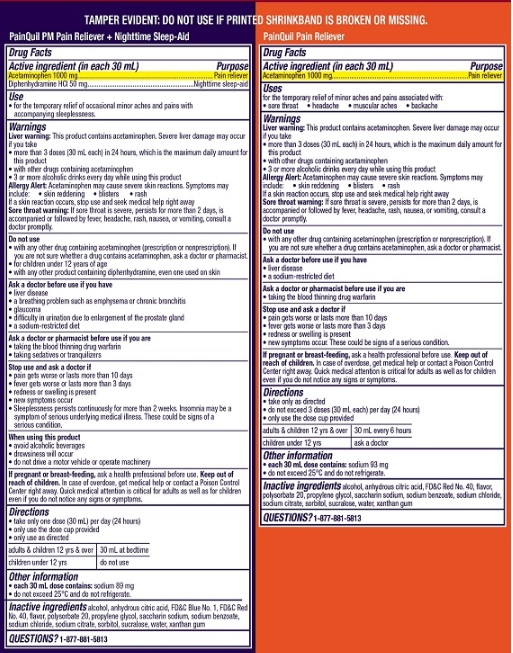 DRUG LABEL: Acetaminophen Liquid / Acetaminophen Diphenhydramine HCl Liquid
NDC: 0363-8757 | Form: KIT | Route: ORAL
Manufacturer: WALGREENS
Category: otc | Type: HUMAN OTC DRUG LABEL
Date: 20251009

ACTIVE INGREDIENTS: ACETAMINOPHEN 1000 mg/30 mL; DIPHENHYDRAMINE HYDROCHLORIDE 50 mg/30 mL; ACETAMINOPHEN 1000 mg/30 mL
INACTIVE INGREDIENTS: SODIUM CHLORIDE; PROPYLENE GLYCOL; GLYCERIN; SODIUM BENZOATE; SACCHARIN SODIUM; POLYETHYLENE GLYCOL, UNSPECIFIED; SORBITOL; POLYSORBATE 20; ANHYDROUS CITRIC ACID; WATER; SODIUM CITRATE, UNSPECIFIED FORM; FD&C RED NO. 40; SUCRALOSE; XANTHAN GUM; FD&C BLUE NO. 1; SORBITOL SOLUTION; SACCHARIN SODIUM; SODIUM BENZOATE; XANTHAN GUM; ANHYDROUS CITRIC ACID; FD&C RED NO. 40; PROPYLENE GLYCOL; WATER; SODIUM CHLORIDE; SUCRALOSE; POLYETHYLENE GLYCOL, UNSPECIFIED; POLYSORBATE 20; SODIUM CITRATE, UNSPECIFIED FORM; GLYCERIN

Walgreens 672L Acetaminophen Liquid (Cherry) + Acetaminophen & Diphenhydramine Liquid (Cherry)

Daytime Pain Reliever

Drug Facts

Active ingredient (in each 30 mL)

Acetaminophen 1000 mg

Purpose

Pain reliever

INDICATIONS AND USAGE

Uses for the temporary relief of minor aches and pains associated with:

- sore throat
- headache
- muscular aches
- backache

Warnings

Liver warning: This product contains acetaminophen. Severe liver damage may occur if you take

- more than 3 doses (30 mL each) in 24 hours, which is the maximum daily amount for this product
- with other drugs containing acetaminophen
- 3 or more alcoholic drinks every day while using this product

Allergy alert: Acetaminophen may cause severe skin reactions. Symptoms may include:

- skin reddening
- blisters
- rash

If a skin reaction occurs, stop use and seek medical help right away.

Sore throat warning: If sore throat is severe, persists for more than 2 days, is accompanied or followed by fever, headache, rash, nausea, or vomiting, consult a doctor promptly.

Do not use

- with any other drug containing acetaminophen (prescription or nonprescription). If you are not sure whether a drug contains acetaminophen, ask a doctor or pharmacist.

Ask a doctor before use if you have

- liver disease
- a sodium-restricted diet

Ask a doctor or pharmacist before use if you are

- taking the blood thinning drug warfarin

Stop use and ask a doctor if

- pain gets worse or lasts more than 10 days
- fever gets worse or lasts more than 3 days
- redness or swelling is present
- new symptoms occur

These could be signs of a serious condition.

PREGNANCY OR BREAST FEEDING

If pregnant or breast-feeding, ask a health professional before use.

Keep out of reach of children. In case of overdose, get medical help or contact a Poison Control Center right away (1-800-222-1222). Quick medical attention is critical for adults as well as for children even if you do not notice any signs or symptoms.

Directions

- take only as directed
- do not exceed 3 doses (30 mL each) per day (24 hours)
- only use the dose cup provided

adults & children 12 yrs & over | 30 mL every 6 hours
children under 12 yrs | ask a doctor

Other information

- each 30 mL contains: sodium 39 mg
- do not exceed 25°C and do not refrigerate.

INACTIVE INGREDIENT

Inactive ingredients anhydrous citric acid, FD&C red no. 40, flavor, glycerin, polysorbate 20, polyethylene glycol, propylene glycol, purified water, saccharin sodium, sodium benzoate, sodium chloride, sodium citrate, sorbitol, sucralose, xanthan gum

Questions or comments? Call 1-877-290-4008

Nighttime Pain Reliever and Sleep Aid

Drug Facts

Active ingredient (in each 30 mL)

Acetaminophen 1000 mg

Diphenhydramine HCl 50 mg

Purpose

Pain reliever

Nighttime sleep-aid

Uses

- for the temporary relief of minor aches and pains associated with accompanying sleeplessness.

Warnings

Liver warning: This product contains acetaminophen. Severe liver damage may occur if you take

- more than 3 doses (30 mL each) in 24 hours, which is the maximum daily amount for this product
- with other drugs containing acetaminophen
- 3 or more alcoholic drinks every day while using this product

Allergy alert: Acetaminophen may cause severe skin reactions. Symptoms may include:

- skin reddening
- blisters
- rash

If a skin reaction occurs, stop use and seek medical help right away.

Sore throat warning: If sore throat is severe, persists for more than 2 days, is accompanied or followed by fever, headache, rash, nausea, or vomiting, consult a doctor promptly.

Do not use

- with any other drug containing acetaminophen (prescription or nonprescription). If you are not sure whether a drug contains acetaminophen, ask a doctor or pharmacist.
- for children under 12 years of age
- with any other product containing diphenhydramine, even one used on skin

Ask a doctor before use if you have

- liver disease
- a breathing problem such as emphysema or chronic bronchitis
- glaucoma
- difficulty in urination due to enlargement of the prostate gland
- a sodium-restricted diet

Ask a doctor or pharmacist before use if you are

- taking the blood thinning drug warfarin
- taking sedatives or tranquilizers

Stop use and ask a doctor if

- pain gets worse or lasts more than 10 days
- fever gets worse or lasts more than 3 days
- redness or swelling is present
- new symptoms occur
- sleeplessness persists continuously for more than 2 weeks.

Insomnia may be a symptom of serious underlying medical illness.

These could be signs of a serious condition.

When using this product

- avoid alcoholic beverages
- drowsiness will occur
- do not drive a motor vehicle or operate machinery

PREGNANCY OR BREAST FEEDING

If pregnant or breast-feeding, ask a health professional before use.

Keep out of reach of children. In case of overdose, get medical help or contact a Poison Control Center right away (1-800-222-1222). Quick medical attention is critical for adults as well as for children even if you do not notice any signs or symptoms.

Directions

- take only one dose (30 mL) per day (24 hours)
- only use the dose cup provided
- only use as directed

adults & children 12 yrs & over | 30 mL at bedtime
children under 12 yrs | do not use

Other information

- each 30 mL contains: sodium 39 mg
- do not exceed 25°C and do not refrigerate.

INACTIVE INGREDIENT

Inactive ingredients anhydrous citric acid, FD&C blue no. 1, FD&C red no. 40, flavor, glycerin, menthol, polyethylene glycol, polysorbate 20, propylene glycol, purified water, saccharin sodium, sodium benzoate, sodium chloride, sodium citrate, sorbitol solution, sucralose, xanthan gum

Questions or comments? Call 1-877-290-4008